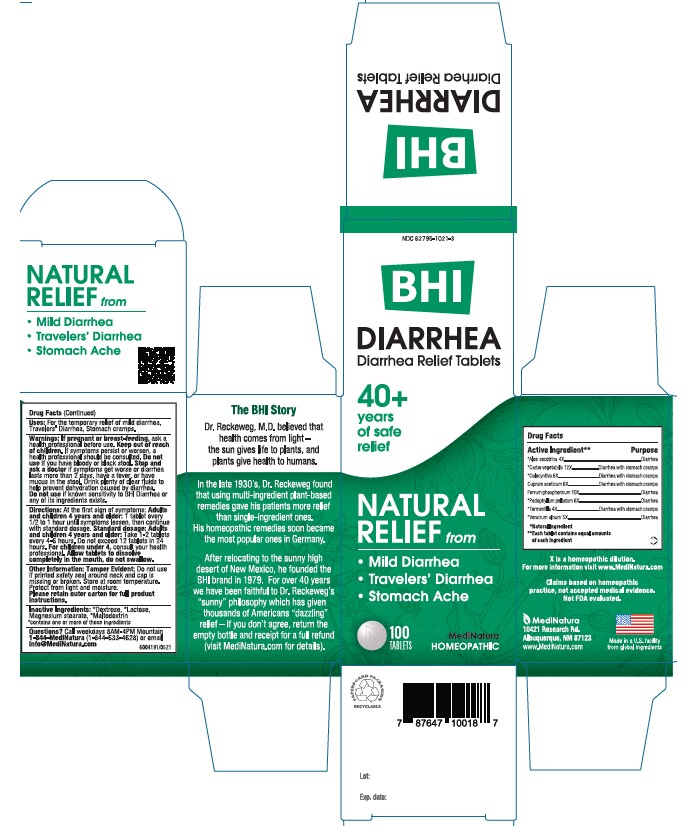 DRUG LABEL: BHI Diarrhea
NDC: 62795-1021 | Form: TABLET
Manufacturer: MediNatura Inc
Category: homeopathic | Type: HUMAN OTC DRUG LABEL
Date: 20230821

ACTIVE INGREDIENTS: ALOE 4 [hp_X]/1 1; ACTIVATED CHARCOAL 12 [hp_X]/1 1; CITRULLUS COLOCYNTHIS FRUIT PULP 6 [hp_X]/1 1; CUPRIC ACETATE 6 [hp_X]/1 1; FERRUM PHOSPHORICUM 10 [hp_X]/1 1; PODOPHYLLUM 6 [hp_X]/1 1; POTENTILLA ERECTA ROOT 4 [hp_X]/1 1; VERATRUM ALBUM ROOT 5 [hp_X]/1 1
INACTIVE INGREDIENTS: LACTOSE; MAGNESIUM STEARATE; MALTODEXTRIN; DEXTROSE

BHI Diarrhea Tablet

ACTIVE INGREDIENTS

Each tablet contains: *Aloe socotrina 4X, *Carbo vegetabilis 12X *Colocynthis 6X, Cuprum aceticum 6X, Ferrum phosphoricum 10X, *Podophyllum peltatum 6X, *Tormentilla 4X, *Veratrum album 5X 37.5 mg each.

*Natural Ingredients

INACTIVE INGREDIENTS

Inactive Ingredients: **Dextrose, ** Lactose, Magnesium Stearate, **Maltodextrin
**contains one or more of these ingredients.

PURPOSE

Diarrhea Relief Tablets

Relieves:

• Diarrhea

• Travelers’ Diarrhea

• Stomach Ache

USES

For the temporary relief of mild diarrhea, travelers’ diarrhea, stomach ache

DIRECTIONS

At first sign of symptoms: Adults and children 4 years and older:

1 tablet every 1/2 to 1 hour until symptoms lessen, then continue with standard dosage.

Standard dosage: Adults and children 4 years and older:

Take 1-2 tablets every 4 to 6 hours. Do not exceed 12 tablets in 24 hours

For children under 4, consult your health professional.

Allow tablets to dissolve completely in the mouth, do not swallow

.

WARNINGS

If pregnant or breast-feeding, ask a health professional before use. Keep out of reach of children. If symptoms persist or worsen, a health professional should be consulted. Do not use if you have bloody or black stool. Stop use and ask a doctor if symptoms get worse or diarrhea lasts more than 2 days, have a fever, or have mucus in the stool. Drink plenty of clear fluids to help prevent dehydration caused by diarrhea. Do not use if known sensitivity to BHI Diarrhea or any of its ingredients exists.

KEEP OUT OF REACH OF CHILDREN